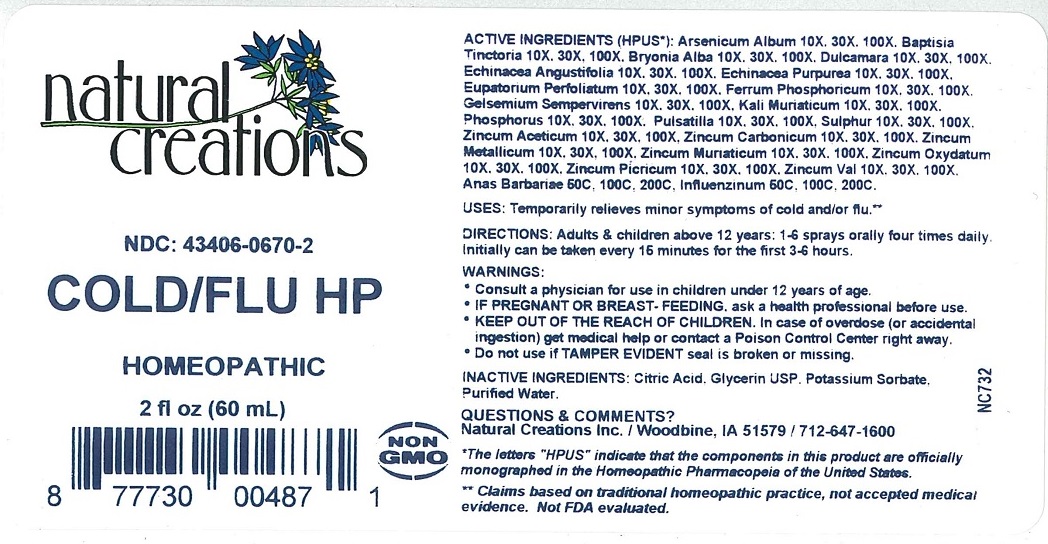 DRUG LABEL: COLD/FLU HP
NDC: 43406-0670 | Form: LIQUID
Manufacturer: Natural Creations, Inc.
Category: homeopathic | Type: HUMAN OTC DRUG LABEL
Date: 20251120

ACTIVE INGREDIENTS: ARSENIC TRIOXIDE 100 [hp_X]/1 mL; BAPTISIA TINCTORIA ROOT 100 [hp_X]/1 mL; BRYONIA ALBA ROOT 100 [hp_X]/1 mL; SOLANUM DULCAMARA TOP 100 [hp_X]/1 mL; ECHINACEA ANGUSTIFOLIA 100 [hp_X]/1 mL; ECHINACEA PURPUREA 100 [hp_X]/1 mL; EUPATORIUM PERFOLIATUM FLOWERING TOP 100 [hp_X]/1 mL; FERROSOFERRIC PHOSPHATE 100 [hp_X]/1 mL; GELSEMIUM SEMPERVIRENS ROOT 100 [hp_X]/1 mL; POTASSIUM CHLORIDE 100 [hp_X]/1 mL; PHOSPHORUS 100 [hp_X]/1 mL; ANEMONE PULSATILLA 100 [hp_X]/1 mL; SULFUR 100 [hp_X]/1 mL; ZINC ACETATE ANHYDROUS 100 [hp_X]/1 mL; ZINC CARBONATE 100 [hp_X]/1 mL; ZINC 100 [hp_X]/1 mL; ZINC CHLORIDE 100 [hp_X]/1 mL; ZINC OXIDE 100 [hp_X]/1 mL; ZINC PICRATE NONAHYDRATE 100 [hp_X]/1 mL; ZINC VALERATE DIHYDRATE 100 [hp_X]/1 mL; CAIRINA MOSCHATA HEART/LIVER AUTOLYSATE 200 [hp_C]/1 mL; INFLUENZA A VIRUS A/SINGAPORE/GP1908/2015 IVR-180 (H1N1) WHOLE 200 [hp_C]/1 mL
INACTIVE INGREDIENTS: CITRIC ACID ACETATE; GLYCERIN; POTASSIUM SORBATE; WATER

COLD/FLU HP

ACTIVE INGREDIENT

ACTIVE INGREDIENTS (HPUS*): Arsenicum Album 10X, 30X, 100X, Baptisia Tinctoria 10X, 30X, 100X,Bryonia Alba 10X, 30X, 100X, Dulcamara 10X, 30X, 100X, Echinacea Angustifolia 10X, 30X, 100X, Echinacea Purpurea 10X, 30X, 100X, Eupatorium Perfoliatum 10X, 30X, 100X, Ferrum Phosphoricum 10X, 30X, 100X, Gelsemium Sempervirens 10X, 30X, 100X, Kali Muriaticum 10X, 30X, 100X, Phosphorus 10X, 30X, 100X, Pulsatilla 10X, 30X, 100X, Sulphur 10X, 30X, 100X, Zincum Aceticum 10X, 30X, 100X, Zincum Carbonicum 10X, 30X, 100X, Zincum Metallicum 10X, 30X, 100X, Zincum Muriaticum 10X, 30X, 100X, Zincum Oxydatum 10X, 30X, 100X, Zincum Picricum 10X, 30X, 100X, Zincum Val 10X, 30X, 100X, Anas Barbariae 50C, 100C, 200C, Influenzinum 50C, 100C, 200C.

PURPOSE

USES: Temporarily relieves minor symptoms of cold and/or flu.**

INDICATIONS AND USAGE

USES: Temporarily relieves minor symptoms of cold and/or flu.**

DOSAGE AND ADMINISTRATION

DIRECTIONS: Adults & childern above 12 years: 1-6 sprays orally four times daily. Initially can be taken every 15 minutes for the first 3-6 hours.

KEEP OUT OF REACH OF CHILDREN

KEEP OUT OF THE REACH OF CHILDREN. In case of overdose (or accidental ingestion) get medical help or contact a Poison Control Center right away.

WARNINGS:

- Consult a physician for use in children under 12 years of age.
- IF PREGNANT OR BREAST-FEEDING, ask a health professional before use.
- KEEP OUT OF THE REACH OF CHILDREN. In case of overdose (or accidental ingestion) get medical help or contact a Poison Control Center right away.
- Do not use if TAMPER EVIDENT seal is broken or missing.

INACTIVE INGREDIENT

INACTIVE INGREDIENTS: Citric Acid, Glycerin USP, Potassium Sorbate, Purified Water.

QUESTIONS

QUESTION & COMMENTS?

Natural Creations Inc. / Woodbine, IA 51579 / 712-647-1600

REFERENCES

*The letters "HPUS" indicate the components in this product are officially monograohed in the Homeopathic Pharmacopeia of the United States.

**Claims based on traditional homeopathic practice, not accepted mediacl evidence. Not FDA evaluated.

PACKAGE LABEL

NDC: 43406-0670-2

COLD/FLU HP

Homeopathic

2 fl oz (60 mL)

877730004871